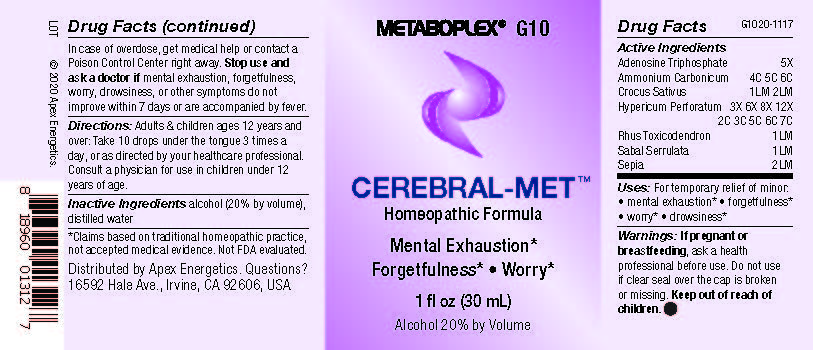 DRUG LABEL: G10
NDC: 63479-0710 | Form: SOLUTION/ DROPS
Manufacturer: Apex Energetics Inc.
Category: homeopathic | Type: HUMAN OTC DRUG LABEL
Date: 20240108

ACTIVE INGREDIENTS: ADENOSINE TRIPHOSPHATE 5 [hp_X]/1 mL; SAFFRON 2 [hp_Q]/1 mL; TOXICODENDRON PUBESCENS LEAF 1 [hp_Q]/1 mL; SEPIA OFFICINALIS JUICE 2 [hp_Q]/1 mL; AMMONIUM CARBONATE 6 [hp_C]/1 mL; HYPERICUM PERFORATUM 7 [hp_C]/1 mL; SAW PALMETTO 1 [hp_Q]/1 mL
INACTIVE INGREDIENTS: ALCOHOL; WATER

G10

Active Ingredients
Adenosine Triphosphate | 5X
Ammonium Carbonicum | 4C 5C 6C
Crocus Sativus | 1LM 2LM
Hypericum Perforatum | 3X 6X 8X 12X 2C 3C 5C 6C 7C
Rhus Toxicodendron | 1LM
Sabal Serrulata | 1LM
Sepia | 2LM

INDICATIONS AND USAGE

Uses:

For temporary relief of minor:

mental exhaustion*

forgetfulness*

worry*

drowsiness*

*Claims based on traditional homeopathic practice, not accepted medical evidence. Not FDA evaluated.

Warnings:

PREGNANCY OR BREAST FEEDING

If pregnant or breastfeeding, ask a health professional before use.

Do not use if clear seal over the cap is broken or missing.

Keep out of reach of children. In case of overdose, get medical help or contact a Poison Control Center right away.

Stop use and ask a doctor if mental exhaustion, forgetfulness, worry, drowsiness, or other symptoms do not improve within 7 days or are accompanied by fever.

Directions:

Adults & children ages 12 years and over: Take 10 drops under the tongue 3 times a day, or as directed by your healthcare professional. Consult a physician for use in children under 12 years of age.

Inactive Ingredients

alcohol (20% by volume), distilled water

Distributed by Apex Energetics. Questions?

16592 Hale Ave., Irvine, CA 92606, USA

PACKAGE LABEL

METABOPLEX® G10

CEREBRAL-MET™

Homeopathic Formula

Mental Exhaustion*

Forgetfulness* Worry*

1 fl oz (30 mL)

Alcohol 20% by Volume